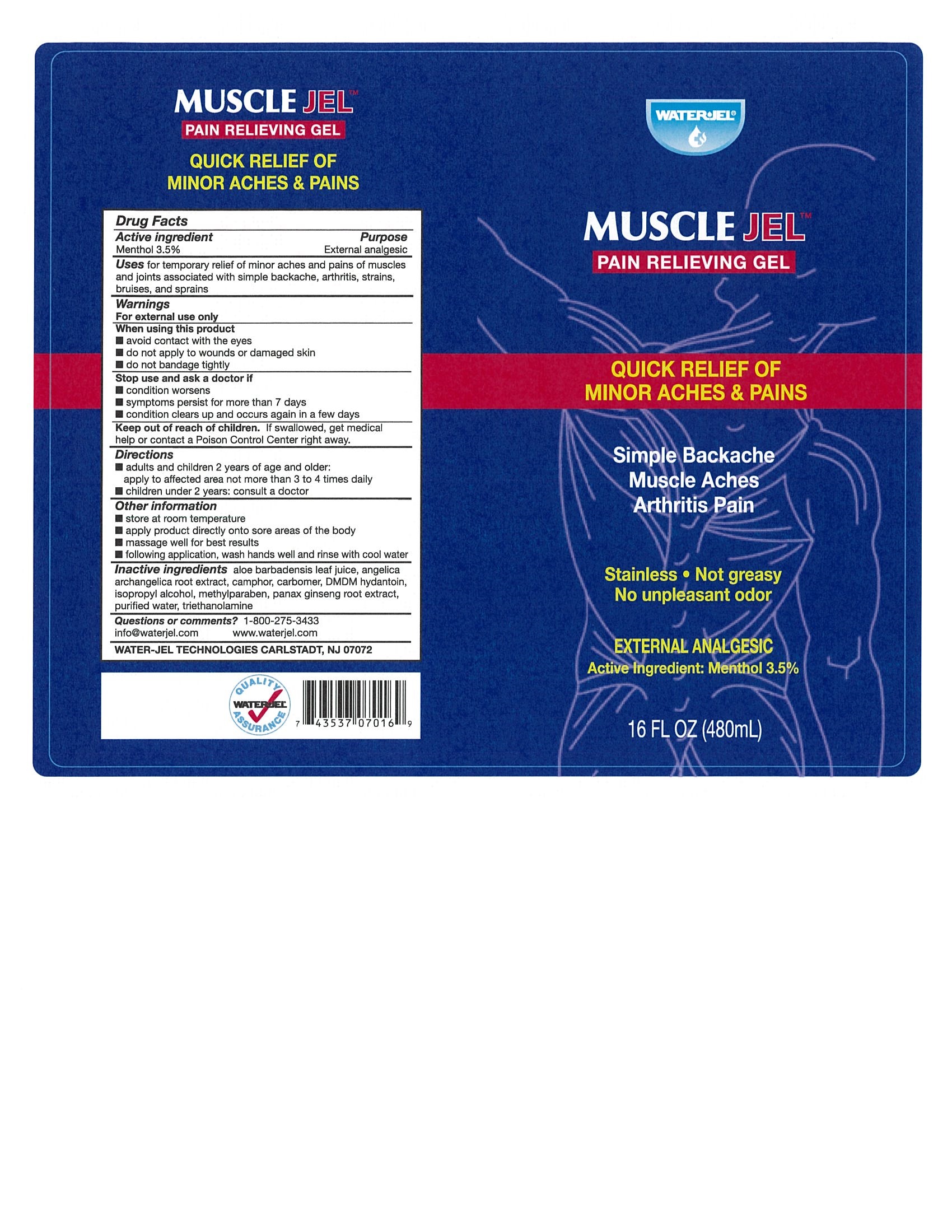 DRUG LABEL: MUSCLE
NDC: 59898-805 | Form: GEL
Manufacturer: WATER-JEL TECHNOLOGIES
Category: otc | Type: HUMAN OTC DRUG LABEL
Date: 20250408

ACTIVE INGREDIENTS: MENTHOL 3.5 g/100 mL
INACTIVE INGREDIENTS: ISOPROPYL ALCOHOL; ANGELICA ARCHANGELICA ROOT; ASIAN GINSENG; ALOE VERA LEAF; CARBOMER HOMOPOLYMER TYPE C; TROLAMINE; DMDM HYDANTOIN; METHYLPARABEN; CAMPHOR (NATURAL); WATER

Muscle Jel

Active ingredient

Menthol 3.5%

Purpose

External analgesic

Uses

for the temporary relief of minor aches and pains of muscles and joints associated with simple backache, arthritis, strains, bruises, and sprains

Warnings

For external use only

When using this product

- avoid contact with the eyes
- do not apply to wounds or damaged skin
- do not bandage tightly

Stop use and ask a doctor if

- conditions worsens
- symptoms persist for more than 7 days
- condition clears up and occurs again within a few days

Keep out of the reach of children

If swallowed, get medical help or contact a Poison Control Center right away

Directions

- adults and children 2 years of age and older: apply to affected area not more than 3 to 4 times daily
- children under 2 years of age: consult a doctor

Other information

- store at room temperature
- apply product directly onto sore areas of the body
- massage well for best results
- following application, wash hands well and rinse with cool water

Inactive ingredients

aloe barbadensis leaf juice, angelica archangelica root extract, camphor, carbomer, DMDM hydantoin, isopropyl alcohol, methylparaben, panax ginseng root extract, purified water, triethanolamine

Questions?

1-800-275-343

info@waterjel.com www.waterjel.com